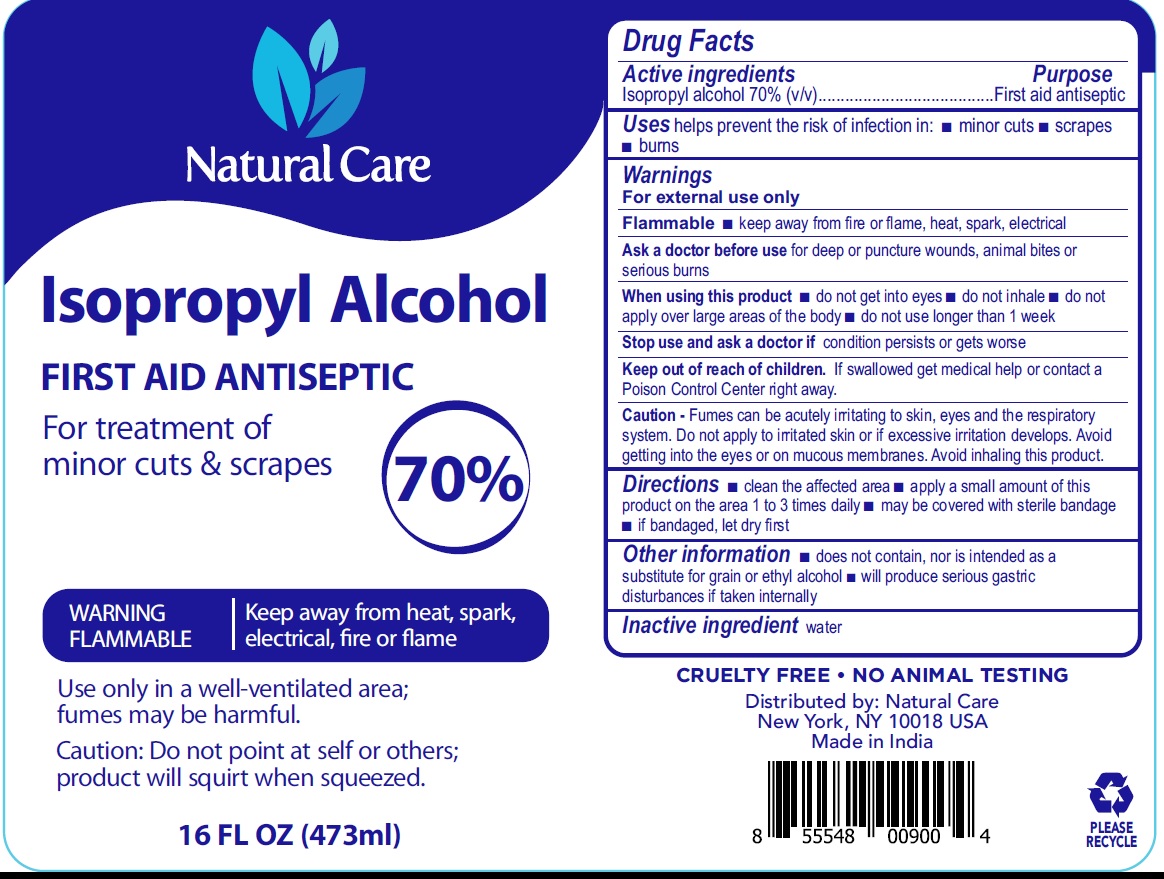 DRUG LABEL: Natural Care Isopropyl Alcohol
NDC: 78261-000 | Form: LIQUID
Manufacturer: Dr. Natural LLC
Category: otc | Type: HUMAN OTC DRUG LABEL
Date: 20200918

ACTIVE INGREDIENTS: ISOPROPYL ALCOHOL 0.7 mL/1 mL
INACTIVE INGREDIENTS: WATER

Natural Care Isopropyl Alcohol

Active ingredients

Isopropyl alcohol 70% (v/v)

Purpose

First aid antiseptic

Uses

helps prevent the risk of infection in:

- minor cuts
- scrapes
- burns

Warnings

For external use only

Flammable

- keep away from fire or flame, heat, spark, electrical

Ask a doctor before use

for deep or puncture wounds, animals bites or serious burns

When using this product

- do not get into eyes
- do not inhale
- do not apply over large areas of the body
- do not use longer then 1 week

Stop use and ask a doctor if

condition persists or gets worse

Keep out of reach of children.

If swallowed get medical help or contact a Poison Control Center right away.

Caution - Fumes can be acutely irritation to skin, eyes and the respiratory system. Do not apply to irritated skin or if excessive irritation develops. Avoid getting into the eyes or on mucous membranes. Avoid inhaling this product

Directions

- clean the affected area
- apply a small amount of this product on the area 1 to 3 times daily
- may be covered with sterile bandage
- if bandaged let dry first.

Other information

- does not contain, nor is intended as a substitute for grain or ethyl alcohol
- will produce serious gastric disturbances if taken internally

Inactive ingredient

water